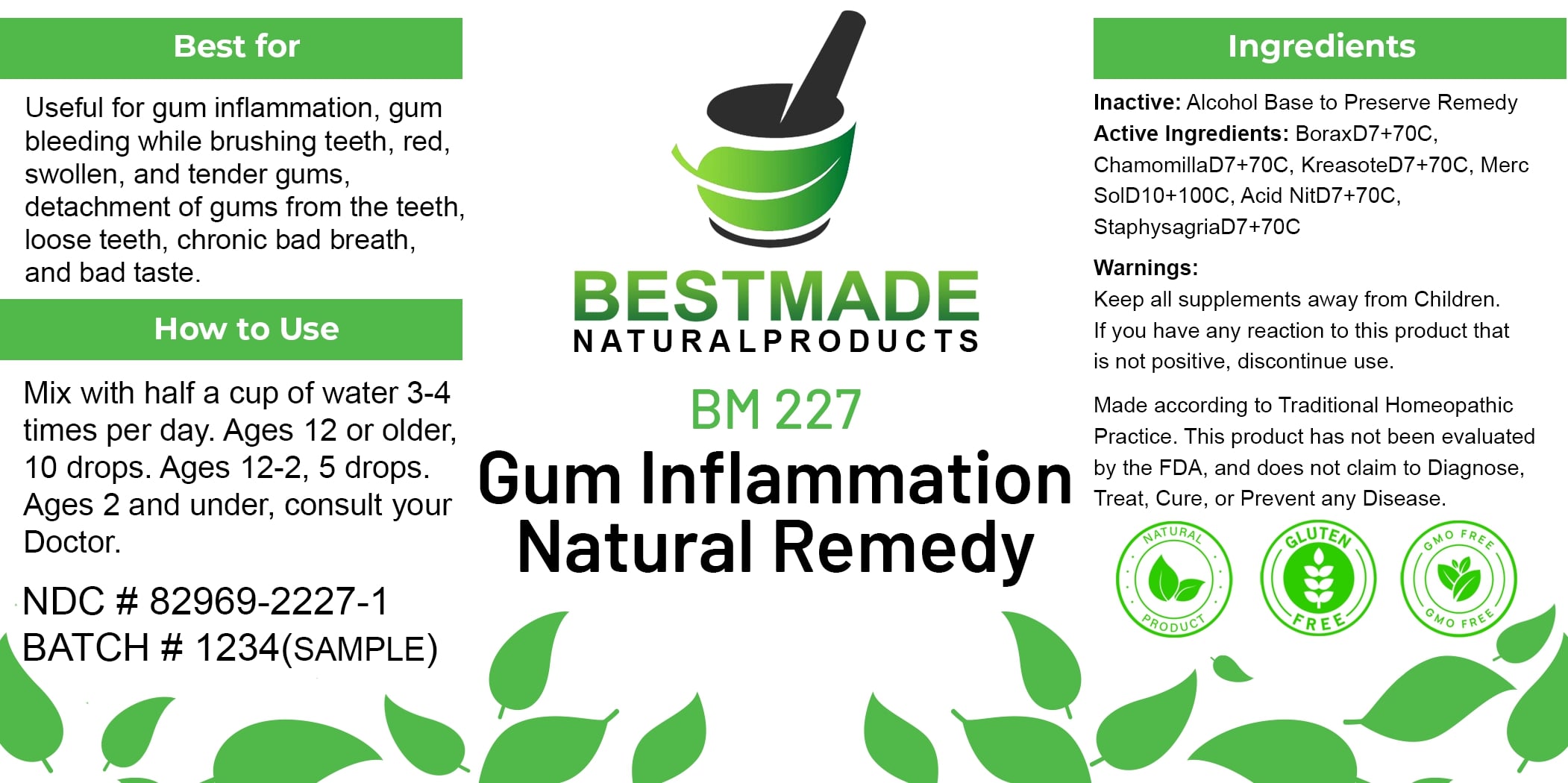 DRUG LABEL: Bestmade Natural Products BM227
NDC: 82969-2227 | Form: LIQUID
Manufacturer: Bestmade Natural Products
Category: homeopathic | Type: HUMAN OTC DRUG LABEL
Date: 20241218

ACTIVE INGREDIENTS: ATROPA BELLADONNA 30 [hp_C]/30 [hp_C]; CHAMOMILE 30 [hp_C]/30 [hp_C]; SODIUM BORATE 30 [hp_C]/30 [hp_C]; MERCURIUS SOLUBILIS 30 [hp_C]/30 [hp_C]; WOOD CREOSOTE 30 [hp_C]/30 [hp_C]; NITRIC ACID 30 [hp_C]/30 [hp_C]; DELPHINIUM STAPHISAGRIA SEED 30 [hp_C]/30 [hp_C]
INACTIVE INGREDIENTS: ALCOHOL 30 [hp_C]/30 [hp_C]

Gum Inflammation (BM227)

DOSAGE AND ADMINISTRATION

Mix with half a cup of water 3-4
times per day. Ages 12 or older,
10 drops. Ages 12-2, 5 drops.
Ages 2 and under, consult your
Doctor.

INDICATIONS AND USAGE

Useful for gum inflammation, gum
bleeding while brushing teeth, red,
swollen, and tender gums,
detachment of gums from the teeth
loose teeth, chronic bad breath,
and bad taste.

Inactive: Alcohol Base to Preserve Remedy

Active Ingredients: BoraxD7+70C
ChamomillaD7+70C. KreasoteD7+70C. Merc
SolD10+100C, Acid NitD7+70C.
StaphysagriaD7+70C

Keep all supplements away from Children.
If you have any reaction to this product that
is not positive, discontinue use.

Made according to Traditional Homeopathic Practice. This product has not been evaluated by the FDA, and does not claim to diagnose, treat, cure, or prevent any disease.

PURPOSE

Useful for gum inflammation, gum
bleeding while brushing teeth, red,
swollen, and tender gums,
detachment of gums from the teeth
loose teeth, chronic bad breath,
and bad taste.

WARNINGS

Keep all supplements away from Children.
If you have any reaction to this product that
is not positive, discontinue use.

Made according to Traditional Homeopathic Practice. This product has not been evaluated by the FDA, and does not claim to diagnose, treat, cure, or prevent any disease.

Entire package label.